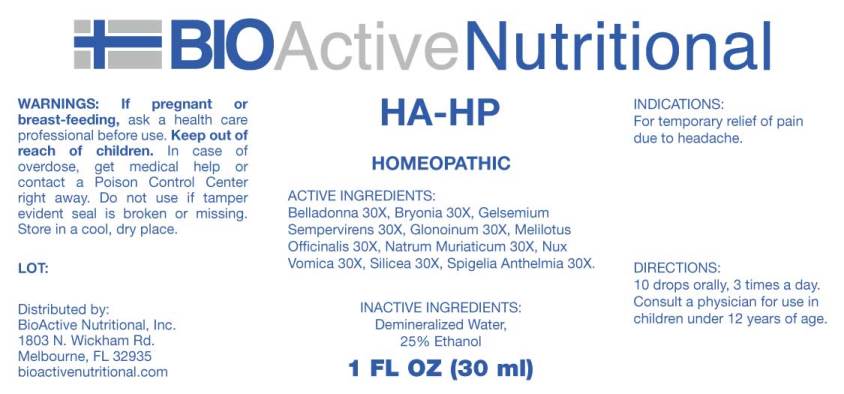 DRUG LABEL: HA HP
NDC: 43857-0285 | Form: LIQUID
Manufacturer: BioActive Nutritional, Inc.
Category: homeopathic | Type: HUMAN OTC DRUG LABEL
Date: 20180706

ACTIVE INGREDIENTS: ATROPA BELLADONNA 30 [hp_X]/1 mL; BRYONIA ALBA ROOT 30 [hp_X]/1 mL; GELSEMIUM SEMPERVIRENS ROOT 30 [hp_X]/1 mL; NITROGLYCERIN 30 [hp_X]/1 mL; MELILOTUS OFFICINALIS TOP 30 [hp_X]/1 mL; SODIUM CHLORIDE 30 [hp_X]/1 mL; STRYCHNOS NUX-VOMICA SEED 30 [hp_X]/1 mL; SILICON DIOXIDE 30 [hp_X]/1 mL; SPIGELIA ANTHELMIA 30 [hp_X]/1 mL
INACTIVE INGREDIENTS: WATER; ALCOHOL

Drug Facts:

ACTIVE INGREDIENTS:

Belladonna 30X, Bryonia (Alba) 30X, Gelsemium Sempervirens 30X, Glonoinum 30X, Melilotus Officinalis 30X, Natrum Muriaticum 30X, Nux Vomica 30X, Silicea 30X, Spigelia Anthelmia 30X.

INDICATIONS:

For temporary relief of pain due to headache.

WARNINGS:

If pregnant or breast-feeding, ask a health care professional before use.

Keep out of reach of children. In case of overdose, get medical help or contact a Poison Control Center right away.

Do not use if tamper evident seal is broken or missing.

Store in cool, dry place.

Keep out of reach of children. In case of overdose, get medical help or contact a Poison Control Center right away.

DIRECTIONS:

10 drops orally, 3 times a day. Consult a physician for use in children under 12 years of age.

INDICATIONS:

For temporary relief of pain due to headache.

INACTIVE INGREDIENTS:

Demineralized water, 25% Ethanol.

QUESTIONS:

Distributed by:
BioActive Nutritional, Inc.
1803 N. Wickham Rd.
Melbourne, FL 32935
bioactivenutritional.com

PACKAGE LABEL DISPLAY:

BIOActive Nutritional

HA-HP

HOMEOPATHIC

1 FL OZ (30 ml)